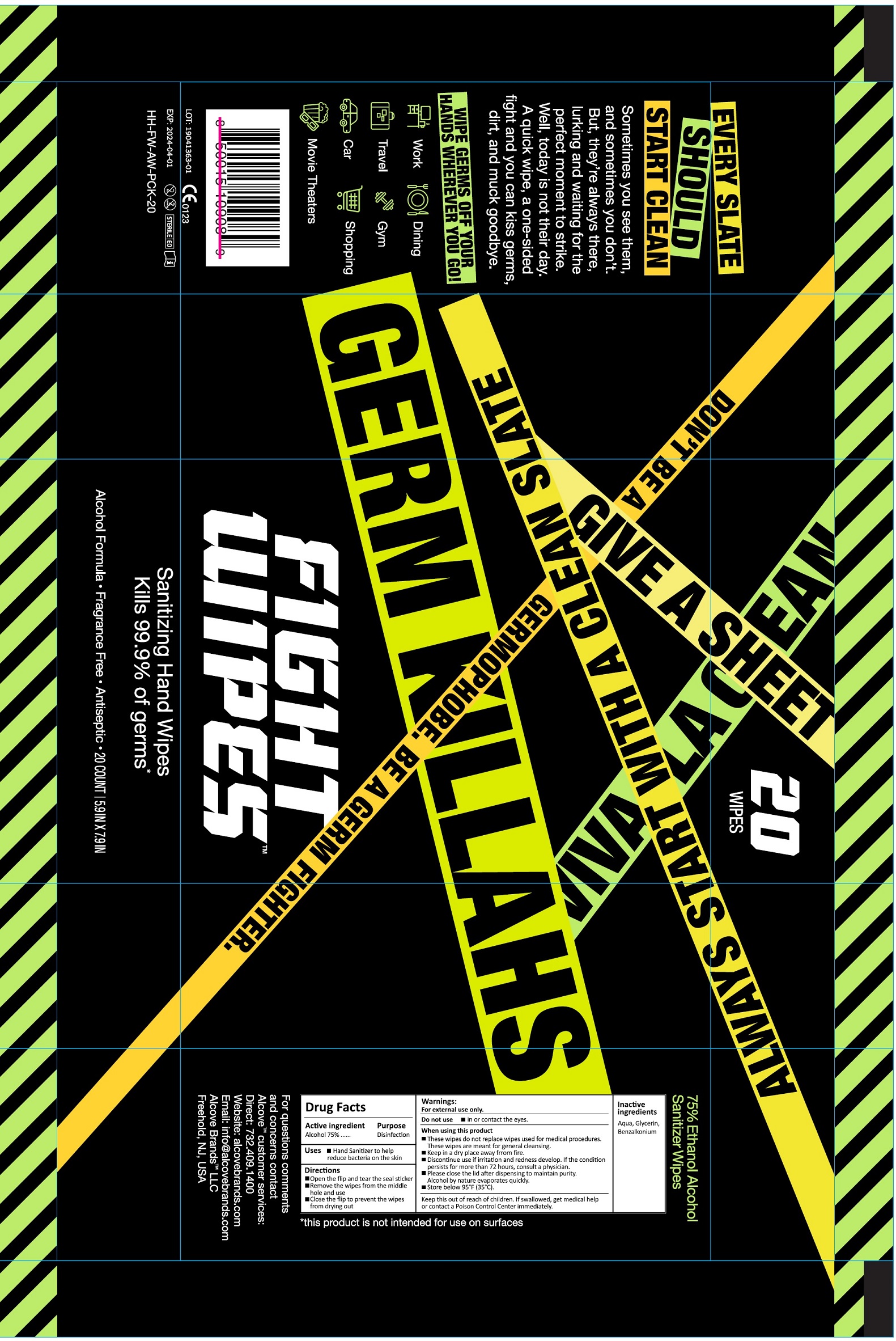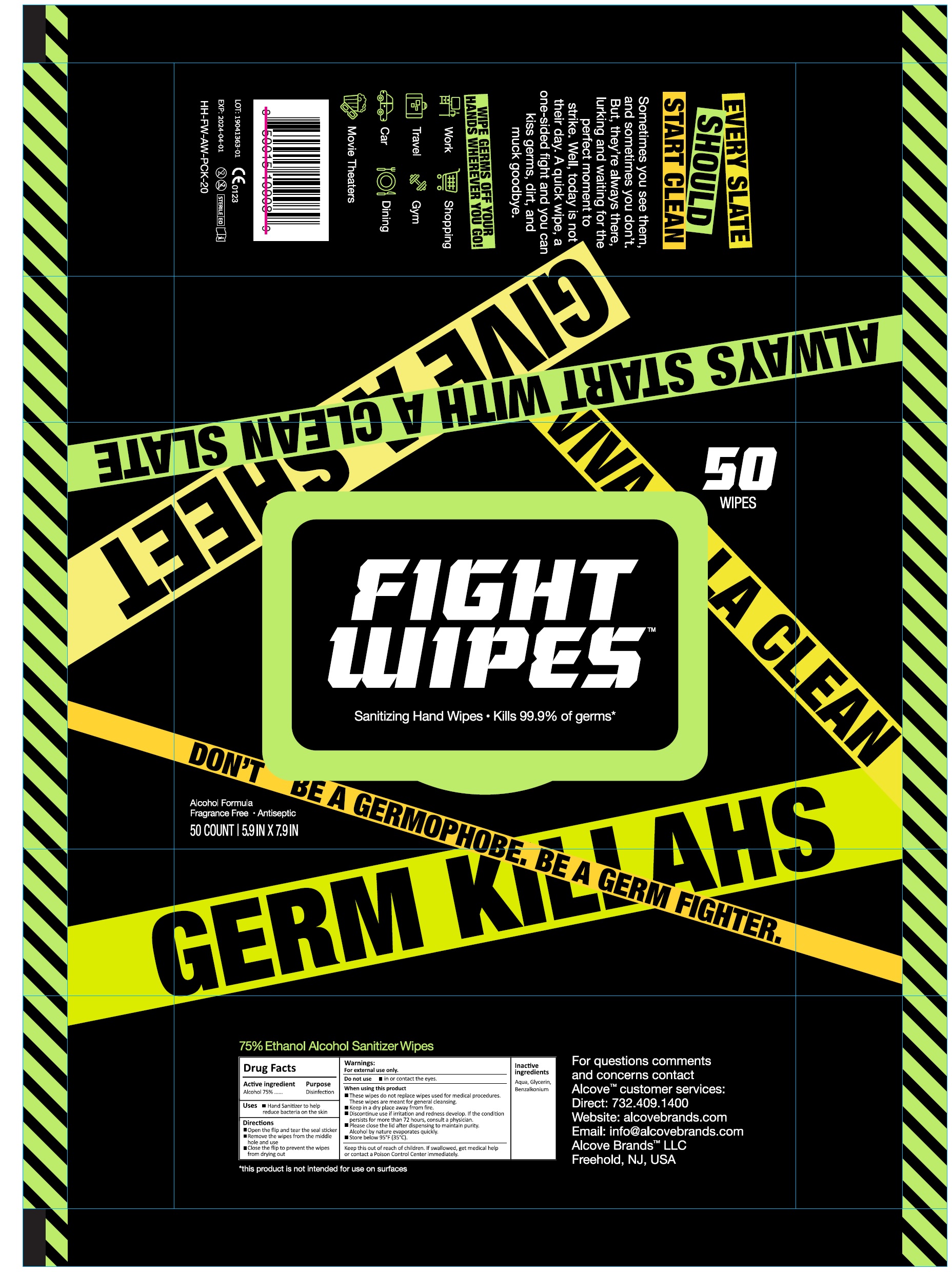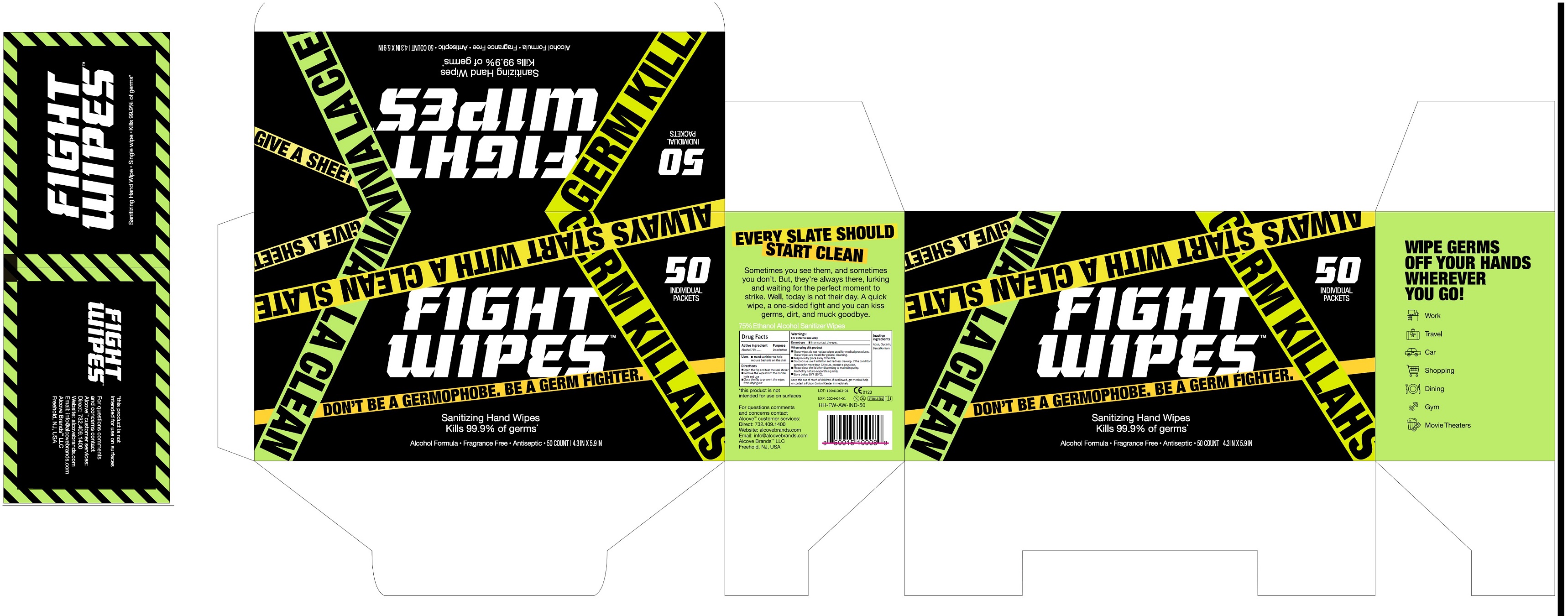 DRUG LABEL: Fight wipes
NDC: 77133-001 | Form: CLOTH
Manufacturer: ALCOVE BRANDS
Category: otc | Type: HUMAN OTC DRUG LABEL
Date: 20250212

ACTIVE INGREDIENTS: ALCOHOL 0.75 mL/1 mL
INACTIVE INGREDIENTS: WATER; GLYCERIN; BENZALKONIUM

Fight wipes

Active ingredient

Alcohol 75%

Purpose

Disinfection

Uses

- Hand Sanitizer to help reduce bacteria on the skin

Directions

- Open the flip and tear the seal sticker
- Remove the wipes from the middle hole and use
- Close the flip to prevent the wipes from drying out

Warnings:

For external use only.

Do not use

- in or contact the eyes.

When using this product

- These wipe do not replace wipe used for medical procedures. These wipes are meant for general cleansing.
- Keep in a dry place away from fire.
- Discontinue use if irritation and redness develop. If the condition persists for more than 72 hours, consult a physician.
- Please close the lid after dispending to maintain purity. Alcohol by nature evaporates quickly.
- Store below 95°F (35°C).

Keep this out of reach of children.

If swallowed, get medical help or contact a Poison Control Center immediately.

Inactive ingredients

Aqua, Glycerin, Benzalkonium